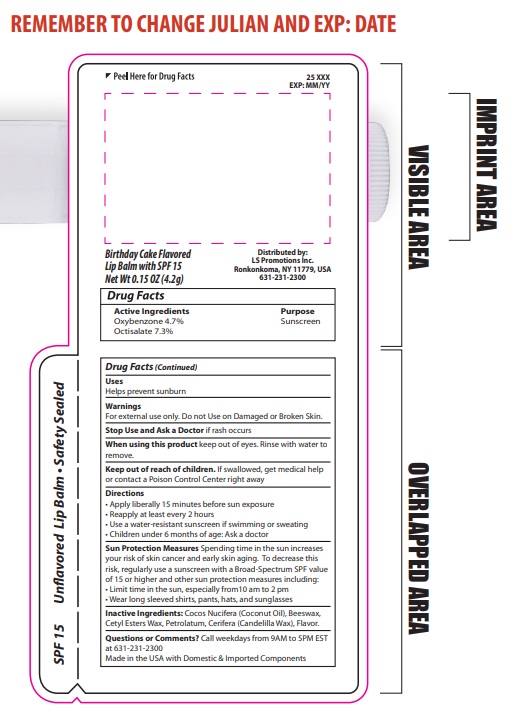 DRUG LABEL: Lip Balm SPF15 Birthday Cake Flavored
NDC: 72449-403 | Form: LIPSTICK
Manufacturer: LS Promotions Inc
Category: otc | Type: HUMAN OTC DRUG LABEL
Date: 20250317

ACTIVE INGREDIENTS: OCTISALATE 0.31 g/4.2 g; OXYBENZONE 0.2 g/4.2 g
INACTIVE INGREDIENTS: COCOS NUCIFERA (COCONUT) OIL; CETYL ESTERS WAX; PETROLATUM; EUPHORBIA CERIFERA (CANDELILLA) WAX; BEESWAX

Lip Balm SPF15 Birthday Cake Flavored

Drug Fact

Drug Facts

Active Ingredients

Oxybenzone 4.7%

Octisalate 7.3%

Purpose

Sunscreen

Uses

Helps prevent sunburn

Warnings

For external use only

Do not Use on Damaged or Broken Skin

Stop Use and Ask a Doctor

If rash occurs

When using this product

Keep out of eyes. Rinse with water to remove.

Keep out of Reach of Children

If swallowed, get medical help or contact a Poison Control Center

Directions

- Apply liberally 15 minutes before sun exposure
- Reapply at least every 2 hours
- Use a water resistant sunscreen if swimming or sweating
- Children under 6 months of age: Ask a doctor

Sun Protection Measures

Spending time in the sun increases your risk of skin cancer and early skin aging. To decrease this risk, regularly use a sunscreen with a Broad Spectrum SPF value of 15 or higher and other sun protection measures including: Limit time in the sun, especially from 10am to 2pm. Wear long sleeved shirts, pants, hats, and sunglasses.

Inactive Ingredients

Cocos Nucifera (Coconut Oil), Beeswax, Cetyl Esters Wax, Petrolatum, Cerifera (Candelilla Wax), Flavor

Questions or Comments

Call weekdays from 9am to 5pm EST at 631-231-2300

Package Label PDP

LB100BDC Lip Balm SPF15 Birthday Cake (NDC 72440-403-01)